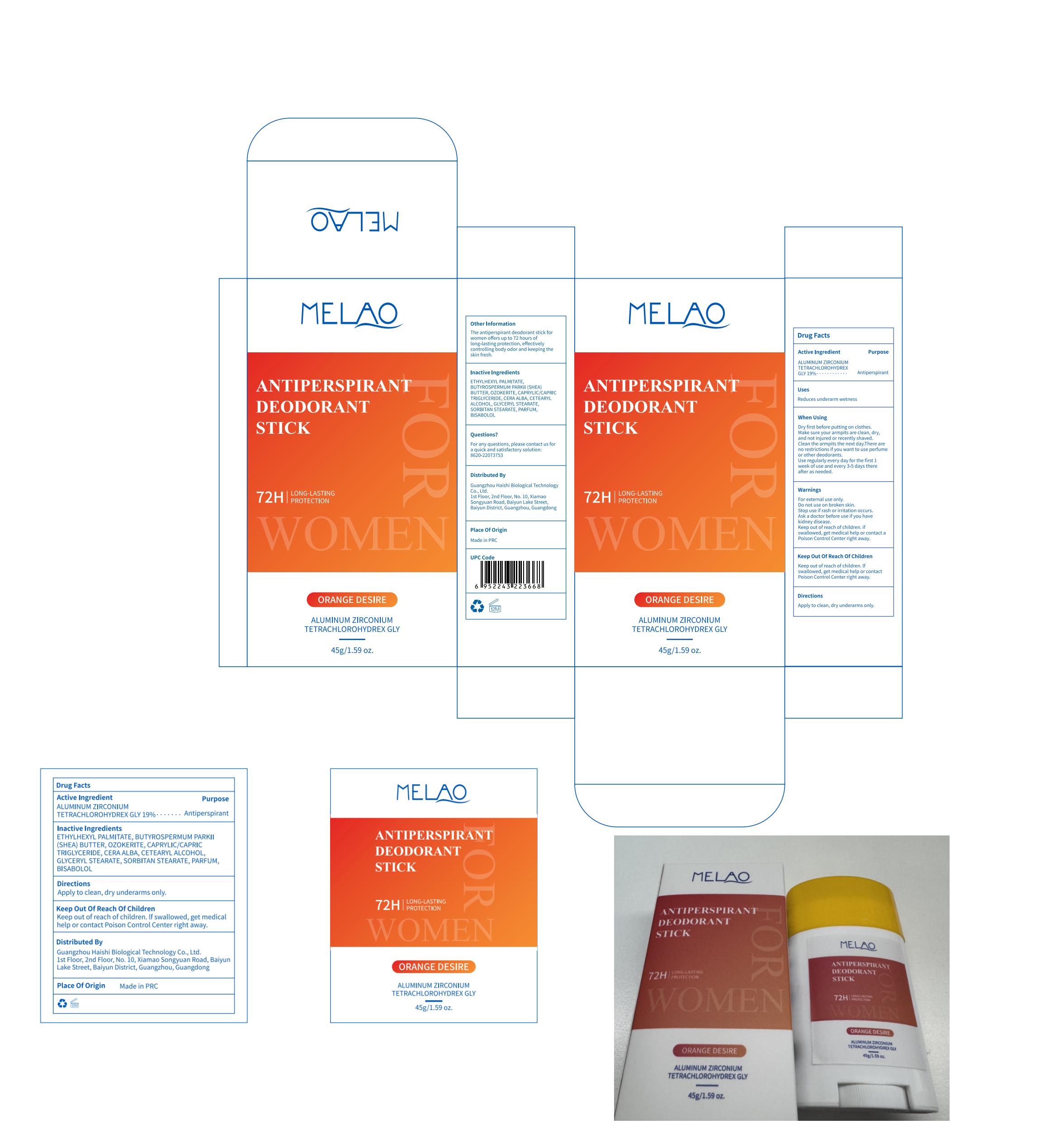 DRUG LABEL: MELAO Antiperspirant Deodorant Stick (orange desire)
NDC: 60771-0019 | Form: STICK
Manufacturer: Guangzhou Haishi Biological Technology Co., Ltd.
Category: otc | Type: HUMAN OTC DRUG LABEL
Date: 20250527

ACTIVE INGREDIENTS: ALUMINUM ZIRCONIUM TETRACHLOROHYDREX GLY 19 g/100 g
INACTIVE INGREDIENTS: CAPRYLIC/CAPRIC TRIGLYCERIDE; ETHYLHEXYL PALMITATE; GLYCERYL STEARATE; BISABOLOL; SORBITAN STEARATE; CETEARYL ALCOHOL

MELAO Antiperspirant Deodorant Stick (orange desire)

ACTIVE INGREDIENT

ALUMINUM ZIRCONIUM TETRACHLOROHYDREX GLY19%

INACTIVE INGREDIENT

OZOKERITE10%
CETEARYL ALCOHOL4%
BUTYROSPERMUM PARKII (SHEA BUTTER)18%
CAPRYLIC/CAPRIC TRIGLYCERIDE10%
ETHYLHEXYL PALMITATE22.9%
GLYCERYL STEARATE4%
SORBITAN STEARATE4%
CERA ALBA6%
BISABOLOL0.1%
PARFUM2%

Do not use on broken skin.

Keep out of reach of children

Stop use if rash or irritation occurs.

WHEN USING

Dry first before putting on clothes.Make sure your armpits are clean, dry,and not iniured or recently shaved.Clean the armpits the next day.Thereare no restrictions if you want to useperfume or other deodorants

WARNINGS

For external use only.

Ask a doctor before use if you havekidney disease.

if swallowed, get medical help or contact a Poison Control Center right away.

PURPOSE

Antiperspirant

DOSAGE AND ADMINISTRATION

Use regularly every day for the first 1week of use and every 3-5 days thereafter as needed.

INDICATIONS AND USAGE

STEP1: Clean and thoroughly dry your skin.

STEP2: Twist the bottom of the product.

STEP3: Gently apply to the underarms or other desired areas.